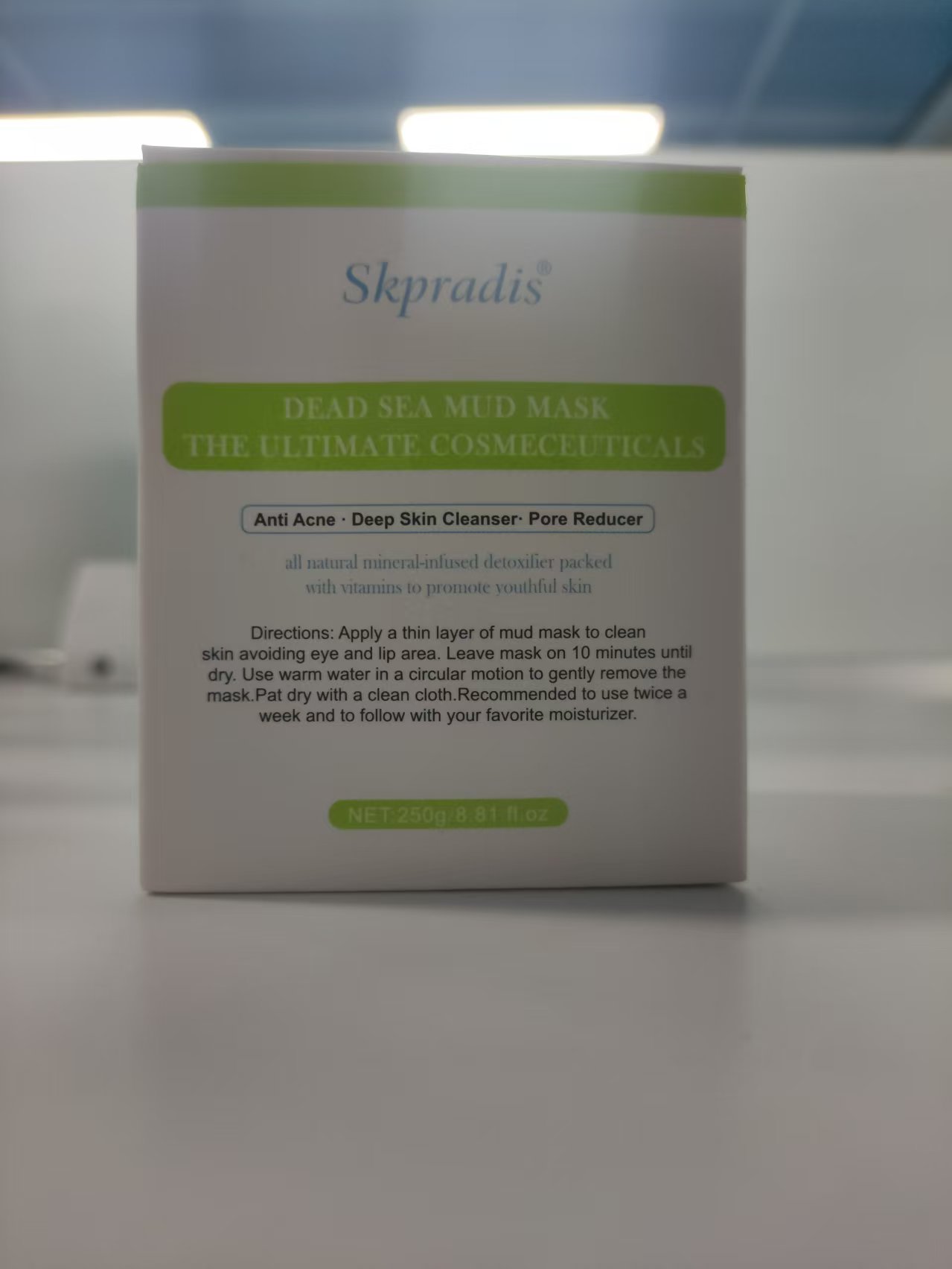 DRUG LABEL: Skpradis Dead Sea Mud Mask
NDC: 84753-018 | Form: EMULSION
Manufacturer: Guangdong Bisutang Biotechnology Co., Ltd.
Category: otc | Type: HUMAN OTC DRUG LABEL
Date: 20241023

ACTIVE INGREDIENTS: KAOLIN 37.5 g/250 g
INACTIVE INGREDIENTS: DIGLYCERIN; MINERAL OIL; CETEARYL ALCOHOL; POLYSORBATE 60; GLYCERYL STEARATE SE; PEG-100 STEARATE; SORBITAN STEARATE; WATER

ACTIVE INGREDIENT

KAOLIN

PURPOSE

After cleansing andtoning, take an appropriate amount ofthis product and apply it evenly on theface, massage until absorbed

Ask Doctor

If you have a history of skin allergies or have sensitive skin, it is advisable to consult a doctor before using this product.

DOSAGE AND ADMINISTRATION

Apply once daily to clean face and neck, avoiding the eye area

WHEN USING

Avoid contact with eyes and broken skin. If redness, swelling, or irritation occurs, discontinue use immediately and seek medical advice.

WARNINGS

Risk InformationFor external use only
Mention de risquesPour usage externe seulement
Do not use on damaged or broken skin.
Ne pas utiliser sur la peau endommagée ou avec des lésions
If rash occurs, discontinue use and consult a health care practitioner.
En présence d'une éruption cutanée, cesser l'utilisation et consulter un praticien de soins de santé
When using this product keep out of eyes. Rinse with water to remove.
Eviter tout contact avec les yeux. Rincer a l'eau le cas échéant
Keep out of reach of children. If swallowed, get medical help or contact a Poison Control Center right away.
Tenir hors de portée des enfants
En cas d'ingestion, consulter un médecin ou appeler un centre antipoison immédiatement.

INDICATIONS AND USAGE

Temporarily protects and helps relieve dry or cracked skin
Beneficlal for face, hands, body, and legs

Keep out of reach of children. If swallowed, get medical help or contact a Poison Control Center right away.
Tenir hors de portée des enfants
En cas d'ingestion, consulter un médecin ou appeler un centre antipoison immédiatement.

INACTIVE INGREDIENT

GLYCERIN
MINERAL OIL
CETEARYL ALCOHOL
POLYSORBATE 60
WATER
GLYCERYL STEARATE
PEG-100 STEARATE
SORBITAN STEARATE
WATER
POLYACRYLAMIDE
C13-14 ISOPARAFFIN
LAURETH-7
WATER
XANTHAN GUM
PHENOXYETHANOL
ALLANTOIN
DIAZOLIDINYL UREA
WATER
METHYLPARABEN
C177266
WATER
PROPYLENE GLYCOL
PHENOXYETHANOL
CAPRYLYL GLYCOL
FRAGRANCE
WATER
BUTYLENE GLYCOL
CENTELLA ASIATICA EXTRACT
PHENOXYETHANOL